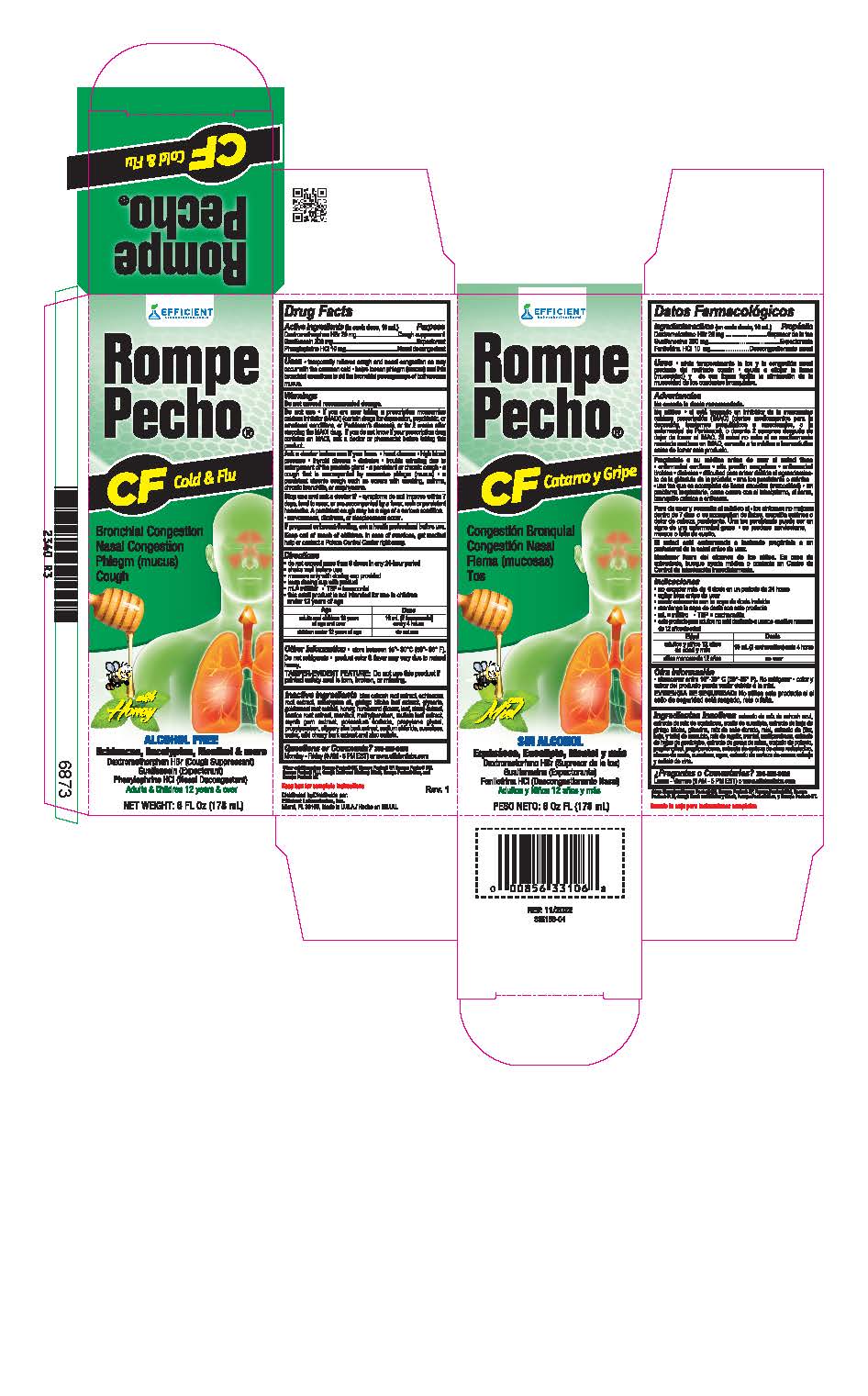 DRUG LABEL: Rompe Pecho
NDC: 58593-235 | Form: LIQUID
Manufacturer: Efficient Laboratories Inc
Category: otc | Type: HUMAN OTC DRUG LABEL
Date: 20250909

ACTIVE INGREDIENTS: DEXTROMETHORPHAN HYDROBROMIDE 10 mg/5 mL; GUAIFENESIN 100 mg/5 mL; PHENYLEPHRINE HYDROCHLORIDE 5 mg/5 mL
INACTIVE INGREDIENTS: HOREHOUND; SUCRALOSE; CAULOPHYLLUM THALICTROIDES ROOT; ECHINACEA, UNSPECIFIED; EUCALYPTUS GLOBULUS LEAF; GINKGO; GOLDENSEAL; HONEY; GLYCYRRHIZA GLABRA; MENTHOL; METHYLPARABEN; VERBASCUM DENSIFLORUM LEAF; MYRRH; POTASSIUM SORBATE; PROPYLENE GLYCOL; PROPYLPARABEN; WATER; ULMUS RUBRA BARK; SODIUM CHLORIDE; PRUNUS SEROTINA BARK; ZINC SULFATE

Drug Facts

Active Ingredients:(in each teaspoonful 5 ml.) Purpose

Dextromethorphan HBr 10 mg ...................................... Cough Suppressant

Guaifenesin 100 mg ................................................................... Expectorant

Phenylephrine HCL 5 mg .................................................... Nasal Decongestant

Purpose

Cough Suppressant

Expectorant

Nasal Decongestant

Warnings

Do not exceed recommended dosage.

Do not use

- If you are taking a prescription monoamine oxidase inhibitor (MAOI) (certain drugs for depression, psychiatric, or
  emotional conditions or Parkinson’s disease), or for 2 weeks after stopping the MAOI drug. If you do not know if your prescription drug contains an MAOI; ask your doctor or pharmacist before taking this product.

Ask a doctor before use if you have
• heart disease

• high blood pressure

• thyroid disease

• diabetes

• trouble urinating due to an enlarged prostate gland

• a persistant or chronic cough

- a cough that is accompanied by excessive phlegm (mucus)

• a breathing problem or chronic cough that lasts or as occurs with smoking, asthma, chronic bronchitis, or emphysema.

Stop use and ask doctor if

- symptoms do not improve within 7 days or is accompanied by a fever, rash, or persistent headache. A persistent cough may be sign of a serious condition.
- nervousness, dizziness, or sleeplessness occurs

PREGNANCY OR BREAST FEEDING

If pregnant or breast-feeding,ask a health professional before use.

Keep out of reach of children. In case of accidental overdose, get medical help or contact a Poison Control Center right away.

Directions

Shake well before use

Do not exceed more than 6 doses in any 24-hour period or as directed by a doctor.

Age | Dose
adults and children 12 years of age and over | 10 mL (2 tsps) every 4 hours
children 6 to under 12 years of age | 5 mL (1 tsp) every 4 hours
children under 6 years of age | consult a doctor

Uses

- temporarily relieves cough and nasal congestion as may occur with the common cold
- helps loosen phlegm (mucus) and thin bronchial secretions to rid the bronchial passageways of bothersome mucus.

INACTIVE INGREDIENT

Inactive Ingredients:Blue Cohosh root extract, Echinacea root extract, Eucalyptus Oil, Ginkgo Biloba leaf extract, glycerin, Golden Seal root extract, Honey, Horehound, Licorice Root extract, Menthol, Methylparaben, Mullein leaf extract, Myrrh gum extract, Potassium Sorbate, Propylene Glycol, Propylparaben, Slippery Elm Bark extract, Sodium Chloride, Sucralose, Water, Wild Cherry Bark extract and Zinc Sulfate.

Questions or Comments?

305-805-3456 Monday - Friday 9AM to 5PM EST

www.efficientlabs.com

Distributed by

Efficient Laboratories, Inc., Miami, Fl 33166

Made in U.S.A.